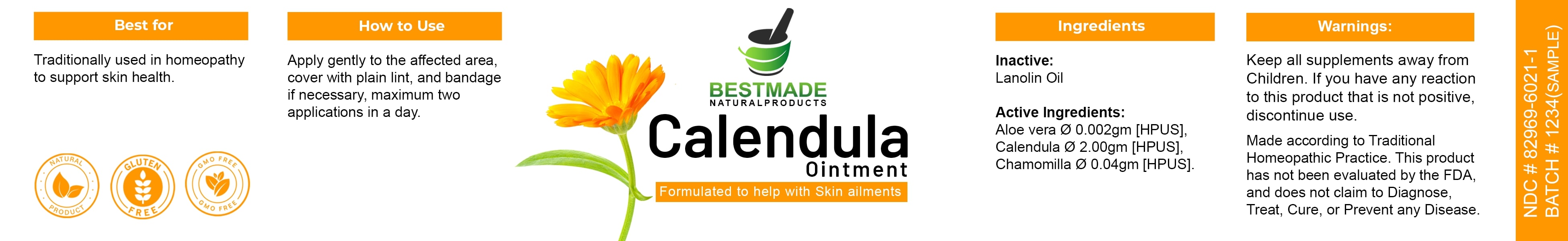 DRUG LABEL: Bestmade Natural Products Calendula
NDC: 82969-6021 | Form: OINTMENT
Manufacturer: Bestmade Natural Products
Category: homeopathic | Type: HUMAN OTC DRUG LABEL
Date: 20241218

ACTIVE INGREDIENTS: CHAMOMILE 4 g/40 g; CALENDULA OFFICINALIS FLOWER 10 g/40 g; ALOE VERA FLOWER 0.002 g/40 g
INACTIVE INGREDIENTS: LANOLIN OIL 40 g/40 g

Calendula Ointment

DOSAGE AND ADMINISTRATION

How to Use

Apply gently to the affected area, cover with plain lint, and bandage if necessary, maximum two applications in a day.

INDICATIONS AND USAGE

Best for

Traditionally used in homeopathy to support skin health.

PURPOSE

Best for

Traditionally used in homeopathy to support skin health.

INACTIVE INGREDIENT

Ingredients

Inactive: Lanolin Oil

Active Ingredients:

Aloe vera 0.002gm [HPUS]

Calendula 2.00gm [HPUS]

Chamomilla 0.04gm [HPUS]

Warnings:

Keep all supplements away from Children.

If you have any reaction to this product that is not positive, discontinue use.

Made according to Traditional Homeopathic Practice. This product has not been evaluated by the FDA, and does not claim to Diagnose, Treat, Cure, or Prevent any Disease.

Warnings:

Keep all supplements away from Children.

If you have any reaction to this product that is not positive, discontinue use.

Made according to Traditional Homeopathic Practice. This product has not been evaluated by the FDA, and does not claim to Diagnose, Treat, Cure, or Prevent any Disease.

Entire package label